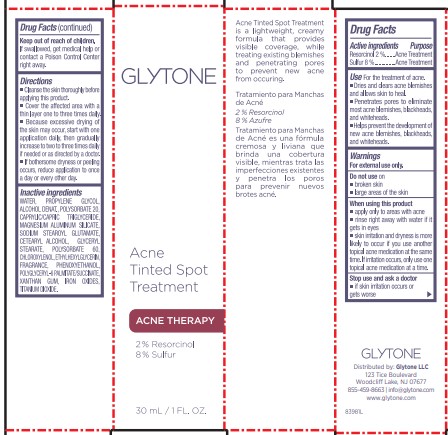 DRUG LABEL: Acne Tinted Spot Treatment
NDC: 84262-023 | Form: LIQUID
Manufacturer: GLYTONE LLC
Category: otc | Type: HUMAN OTC DRUG LABEL
Date: 20241217

ACTIVE INGREDIENTS: SULFUR 0.08 mg/1 1; TITANIUM DIOXIDE 0.02 mg/1 1
INACTIVE INGREDIENTS: POLYSORBATE 60; CHLOROXYLENOL; PROPYLENE GLYCOL; CETEARYL ALCOHOL; MAGNESIUM ALUMINUM SILICATE; SODIUM STEAROYL GLUTAMATE; IRON OXIDES; PHENOXYETHANOL; FARNESOL; CAPRYLIC/CAPRIC TRIGLYCERIDE; XANTHAN GUM; POLYGLYCERYL-4 PALMITATE; WATER; GLYCERYL STEARATE; ALCOHOL; ETHYLHEXYLGLYCERIN

Glytone Acne Tinted Spot Treatment

Active Ingredients

Resorcinol 2%

Sulfur 8%

Purpose

Acne Treatment

Use

For the treatment of acne.

- Dries and clears acne blemishes and allows skin to heal.
- Penetrates pores to eliminate most acne blemishes, blackheads, and whiteheads.
- Helps prevent the development of new acne blemishes, blackheads, and whiteheads.

Warnings

For external use only.

When using this product

- apply only to areas with acne
- rinse right away with water if it gets in eyes
- skin irritation and dryness is more likely to occur if you use another topical acne medication at the same time. If irritation occurs, only use one topical acne medication at a time.

Stop use and ask a doctor

- if skin irritation occurs or gets worse

Keep out of reach of children

If swallowed, ge medical help or contact a Poison Control Center right away.

Do not use

on

- broken skin
- large areas of the skin

Directions

- Cleanse the skin thoroughly before applying this product.
- Cover the affected area with a thin layer one to three times daily.
- Because excessive drying of the skin may occur, start with one application daily, then gradually increase to two to three times daily if needed or as directed by a doctor.
- If bothersome dryness or peeling occurs, reduce application to once a day or every other day.

Inactive Ingredients

WATER, PROPYLENE GLYCOL. ALCOHOL DENAT., POLYSORBATE 20, CAPRYLIC/CAPRIC TRIGLYCERIDE, MAGNESIUM ALUMINUM SILICATE, SODIUM STEAROYL, GLUTAMATE, CETEARYL ALCOHOL, GLYCERYL SEARATE, POLYSORBATE 60, CHLOROXYLENOL, ETHYLHEXYLGLYCERIN, FRAGRANCE, PHENOXYETHANOL, POLYGLYCERYL-6 PALMITATE.SUCCINATE, XANTHAN GUM, IRON OXIDES, TITANIUM DIOXIDE

Principal Display Panel

GLYTONE

ACNE TINTED SPOT TREATMENT

ACNE THERAPY

2% RESORCINOL

8% SULFURE

30ML / 1 FL. OZ.